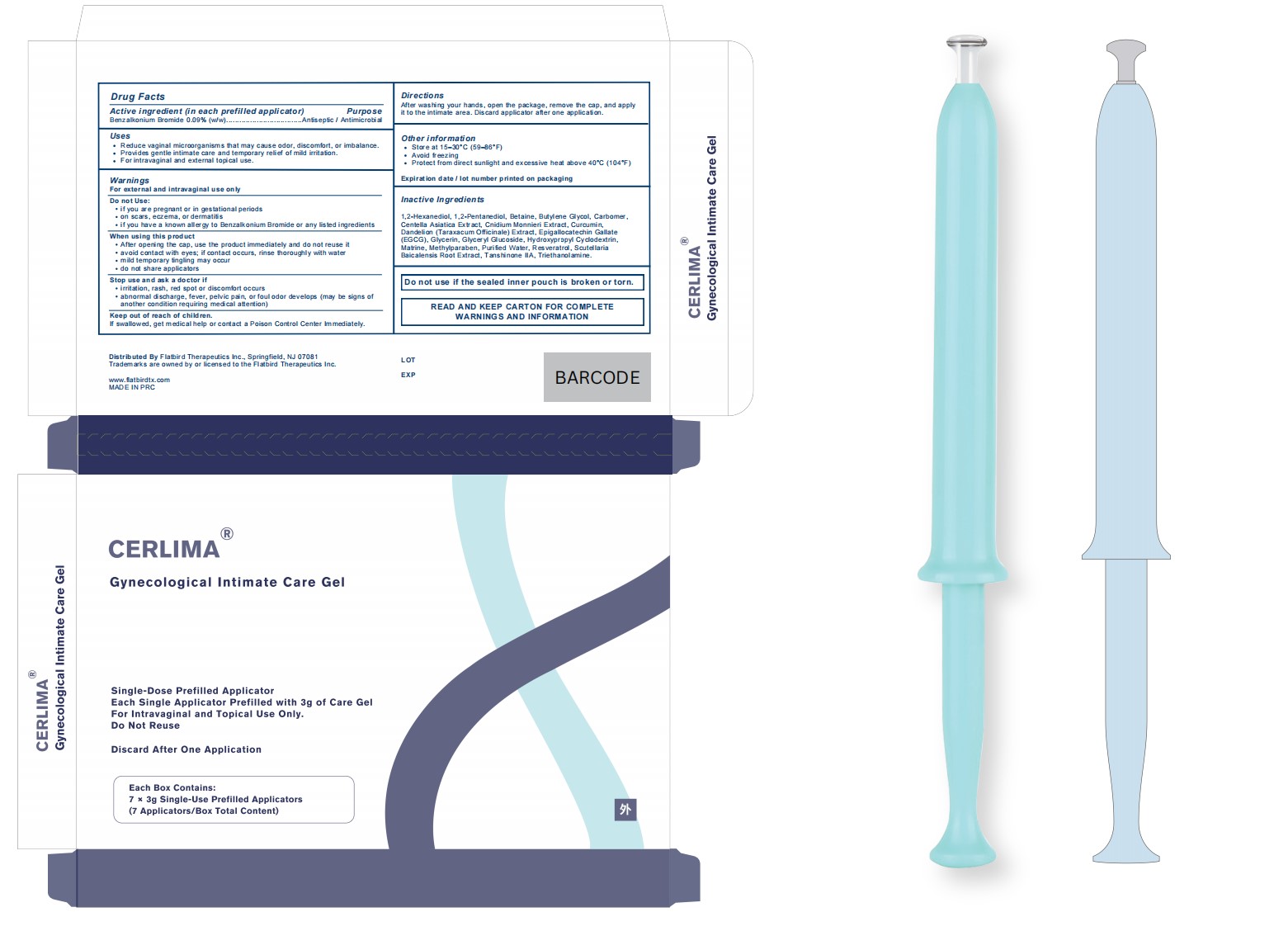 DRUG LABEL: CERLIMA
NDC: 73813-0001 | Form: GEL
Manufacturer: Guangzhou Zhongkebaishi Health Industry CO., LTD
Category: otc | Type: HUMAN OTC DRUG LABEL
Date: 20260116

ACTIVE INGREDIENTS: BENZALKONIUM BROMIDE 0.09 g/100 g
INACTIVE INGREDIENTS: CNIDIUM MONNIERI FRUIT OIL; TANSHINONE IIA; WATER; BUTYLENE GLYCOL; GLYCERIN; 1,2-HEXANEDIOL; CARBOMER; TRIETHANOLAMINE; MATRINE; PENTYLENE GLYCOL; METHYLPARABEN; GLYCERYL GLUCOSIDE; EPIGALLOCATECHIN GALLATE; SCUTELLARIA BAICALENSIS WHOLE; CENTELLA ASIATICA; CURCUMIN; TARAXACUM OFFICINALE; RESVERATROL; BETAINE; HYDROXYPROPYL BETADEX

73813-0001

Active Ingredient(s)

Benzalkonium Bromide 0.09%

Purpose

Antiseptic / Antimicrobial

Use

1.Reduce vaginal microorganisms that may cause odor, discomfort, or imbalance

2.Provides gentle intimate care and temporary relief of mild irritation.

3.For intravaginal and external topical use.

Warnings

For external and intravaginal use only

Do not use

1. if you are pregnant or in gestational periods
2. on scars, eczema, or dermatitis
3. if you have a known allergy to Benzalkonium Bromide or any listed ingredients

WHEN USING

1. After opening the cap, use the product immediately and do not reuse it.

2. avoid contact with eyes; if contact occurs, rinse thoroughly with water
3. mild temporary tingling may occur
2. do not share applicators

STOP USE

1. irritation, rash, red spot or discomfort occurs .

2.abnormal discharge, fever, pelvic pain, or foul odor develops (may be signs ofanother condition requiring medical attention)

KEEP OUT OF REACH OF CHILDREN

If swallowed, get medical help or contact a Poison Control Center Immediately.

Directions

After washing your hands, open the package, remove the cap, and applyit to the intimate area. Discard applicator after one application.

Other information

1. Store at 15-30°C(59-86°F)
2. Avoid freezing

3. Protect from direct sunlight and excessive heat above 40°C (104°F)

Inactive ingredients

1,2-Hexanediol, 1,2-Pentanediol, Betaine, Butylene Glycol, Carbomer,Centella Asiatica Extract, Cnidium Monnieri Extract, Curcumin,Dandelion (Taraxacum Officinale) Extract, Epigallocatechin GallateEGG Grerfar abereIGlee taee'NeovSPerfoY,'SCuferferarin.Baicalensis Root Extract, Tanshinone IA, Triethanolamine.